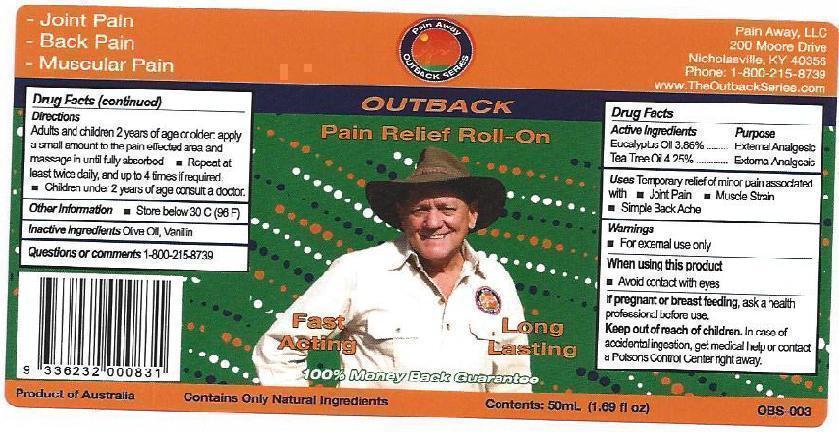 DRUG LABEL: Out Back Pain Relief
NDC: 69594-001 | Form: OIL
Manufacturer: Ultra Mix (Aust) Pty Ltd 
Category: otc | Type: HUMAN OTC DRUG LABEL
Date: 20160408

ACTIVE INGREDIENTS: EUCALYPTUS OIL 38.6 mg/1 mL; TEA TREE OIL 42.5 mg/1 mL
INACTIVE INGREDIENTS: OLIVE OIL; VANILLIN

Out Back Pain Relief

Actives

Tea Tree Oil (Melaleuca Alternifolia) - 4.25% (42.5 mg/ml)
Eucalyptus Oil (Eucalyptus radiata) - 3.86% (38.6 mg/ml)

Inactives

Olive oil and Vanilin

Purpose

Massage Oil to assist with relief of joint and muscle pain

Indication and Usage

Temporary relief of joint and muscle pain, including lower back pain

Dosage and Administration

Apply a small amount of Elmore Oil to the pain affected area and gently massage in until fully absorbed. Use before and after activity for maximum relief.

Warnings

For external use only.

In case of accidental ingestion, get medical help or contact a Poisons Control Center right away.

If pregnant or breast feeding ask health care professional before use.

Keep out of reach from children.

Keetp out of reach of children